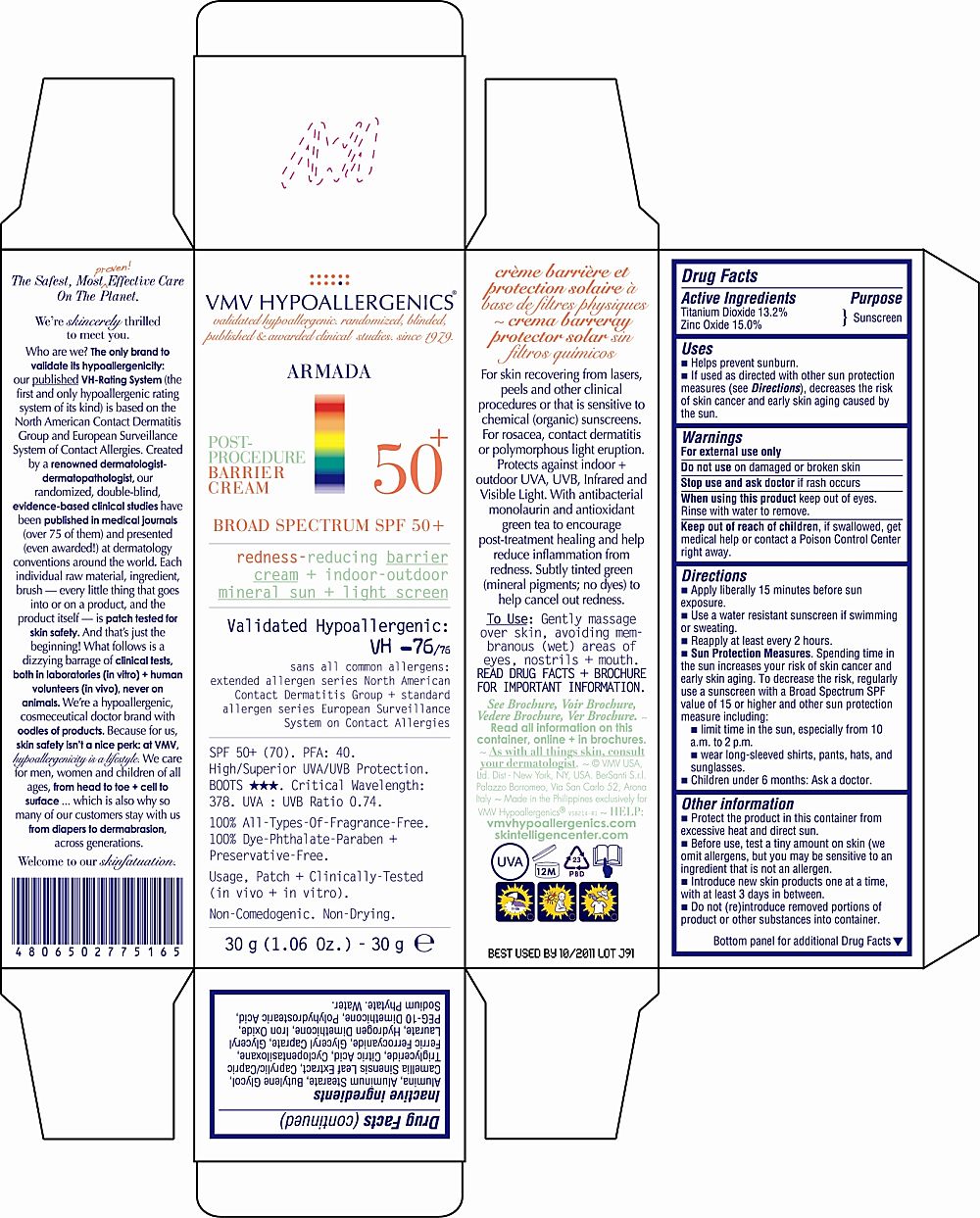 DRUG LABEL: VMV HYPOALLERGENICS ARMADA POST PROCEDURE 50 PLUS
NDC: 69774-163 | Form: CREAM
Manufacturer: SKIN SCIENCES LABORATORY INC.
Category: otc | Type: HUMAN OTC DRUG LABEL
Date: 20150914

ACTIVE INGREDIENTS: TITANIUM DIOXIDE 13.2 g/30 g; ZINC OXIDE 15 g/30 g
INACTIVE INGREDIENTS: WATER

Uses

- Helps prevent sunburn.

- If used as directed with other sun protection measures (see Directions), decrease the risk of skin cancer and early skin aging caused by the sun.

Warnings

For External use only

Do not use on damagae skin or broken skin

Stop use and ask doctor if rash occurs

When using this product keep out of eyes. Rinse with water to remove.

Keep out of reach of children, if swallowed, get medical help or contact a Poison Control Center right away.

Directions

- Apply liberally 15 minutes before sun exposure

- Use a water resistant sunscreen if swimming or sweating.

- Reapply at leats every 2 hours

- Sun Proctection Measures. Spending time in the sun increases your risk of skin cancer and early skin aging. To decrease the risk, regularly use a sunscreen with a Broad Spectrum SPF value of 15 or higher and other sun protection measure including:

- Limit time in the sun, especiallly from 10am to 2pm

- Wear long-sleeved shirts, pants, hats, and sunglasses.

- Children under 6months: Ask a doctor.

Other Information

- Protect the product in this container from excessive heat and direct sun

- Before use, test a tiny amount on skin (we omit allergen, but you may be sensitive to an ingredient that is not an allergen.)

- Introduce new skin products one at a time, with atleast 3 days in between.

- Do not (re)introduce removed portions of products or other substances into container.

Inactive Ingredients

Alumina, Aluminum Stearate, Butylene Glycol, Camellia Sinensis Leaf Extract, Caprylic/Capric Triglyceride, Citric Acid, Cyclopentasiloxane, Ferric Ferrocyanide, Glyceryl Caprate, Glyceryl Laurate, Hydrogen Dimethicone, Iron Oxide, PEG-10 Dimethicone, Polyhydrostearic Acid, Sodium Phytate, Water.

Principal Display Panel

VMV HYPOALLERGENICS

validated hypoallergenics randomized blinded

published & awarded clinical studies since 1979

ARMADA

POST-

PROCEDURE

BARRIER

CREAM

50+

BROAD SPECTRUM SPF 50+

rednedd-reducing barrier cream + indoor-outdoor

mineral sun+light screen

Validated Hypoallergenic:

VH -76/76

sans all common allergens:

extended allergen series North American

Contact Dermatitis Group + standard

allergenc series European Surveillance

System on Contact Allergies

SPF 50+ (70). PFA: 40.

High/Superior UVA/UVB Protection.

BOOTS (3 stars). Critical Wavelength:

378. UVA:UVB Ratio 0.74.

100% All-Types-Of-Fragrance-Free.

100% Dye-Phthalate-Paraben +

Preservative Free.

Usage, Patch + Clinically-Tested

(in-vitro + in-vivo).

Non-Comedogenic. Non-Drying.

30g (1.06 Oz.) - 30g e